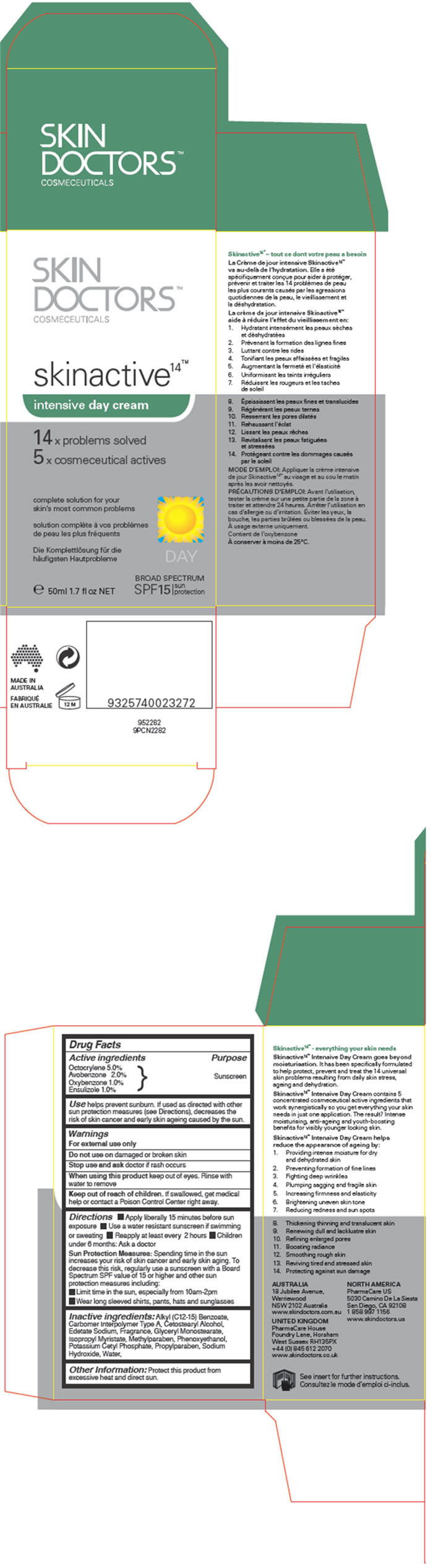 DRUG LABEL: Skin Active 
NDC: 49203-710 | Form: CREAM
Manufacturer: Cat Media Pty Ltd
Category: otc | Type: HUMAN OTC DRUG LABEL
Date: 20120202

ACTIVE INGREDIENTS: Octocrylene 49.7 mg/1 mL; Avobenzone 19.9 mg/1 mL; Oxybenzone 9.9 mg/1 mL; Ensulizole 9.9 mg/1 mL
INACTIVE INGREDIENTS: Alkyl (C12-15) Benzoate; Phenoxyethanol; Water; Glyceryl Monostearate; Methylparaben; Propylparaben; Sodium hydroxide; Cetostearyl alcohol; Isopropyl myristate; Potassium cetyl phosphate; Carbomer homopolymer Type C; Edetate Sodium

Skin Active^14™ Intensive Day Cream

Drug Facts

ACTIVE INGREDIENT

Active ingredients | Purpose
Octocrylene 5.0%
Avobenzone 2.0% | Sunscreen
Oxybenzone 1.0% | Sunscreen
Ensulizole 1.0%

Use

helps prevent sunburn. If used as directed with other sun protection measures (see Directions), decreases the risk of skin cancer and early skin ageing caused by the sun.

Warnings

For external use only

Do not use on damaged or broken skin

STOP USE

Stop use and ask doctor if rash occurs

When using this product keep out of eyes. Rinse with water to remove

Keep out of reach of children. If swallowed, get medical help or contact a Poison Control Center right away.

Directions

- Apply liberally 15 minutes before sun exposure
- Use a water resistant sunscreen if swimming or sweating
- Reapply at least every 2 hours
- Children under 6 months: Ask a doctor

Sun Protection Measures:

Spending time in the sun increases your risk of skin cancer and early skin aging. To decrease this risk, regularly use a sunscreen with a Board Spectrum SPF value of 15 or higher and other sun protection measures including:

- Limit time in the sun, especially from 10am-2pm
- Wear long sleeved shirts, pants, hats and sunglasses

Inactive ingredients

Alkyl (C12-15) Benzoate, Carbomer Interpolymer Type A, Cetostearyl Alcohol, Edetate Sodium, Fragrance, Glyceryl Monostearate, Isopropyl Myristate, Methylparaben, Phenoxyethanol, Potassium Cetyl Phosphate, Propylparaben, Sodium Hydroxide, Water,

Other Information

Protect this product from excessive heat and direct sun.

NORTH AMERICA
PharmaCare US
5030 Camino De La Siesta
San Diego, CA 92108

PRINCIPAL DISPLAY PANEL - 50ml Bottle Carton

SKIN
DOCTORS™
COSMECEUTICALS

skinactive^14™

intensive day cream

14 × problems solved

15 × cosmeceutical actives

complete solution for your
skin's most common problems

e 50ml 1.7 fl oz NET

DAY

BROAD SPECTRUM
SPF15
sun
protection